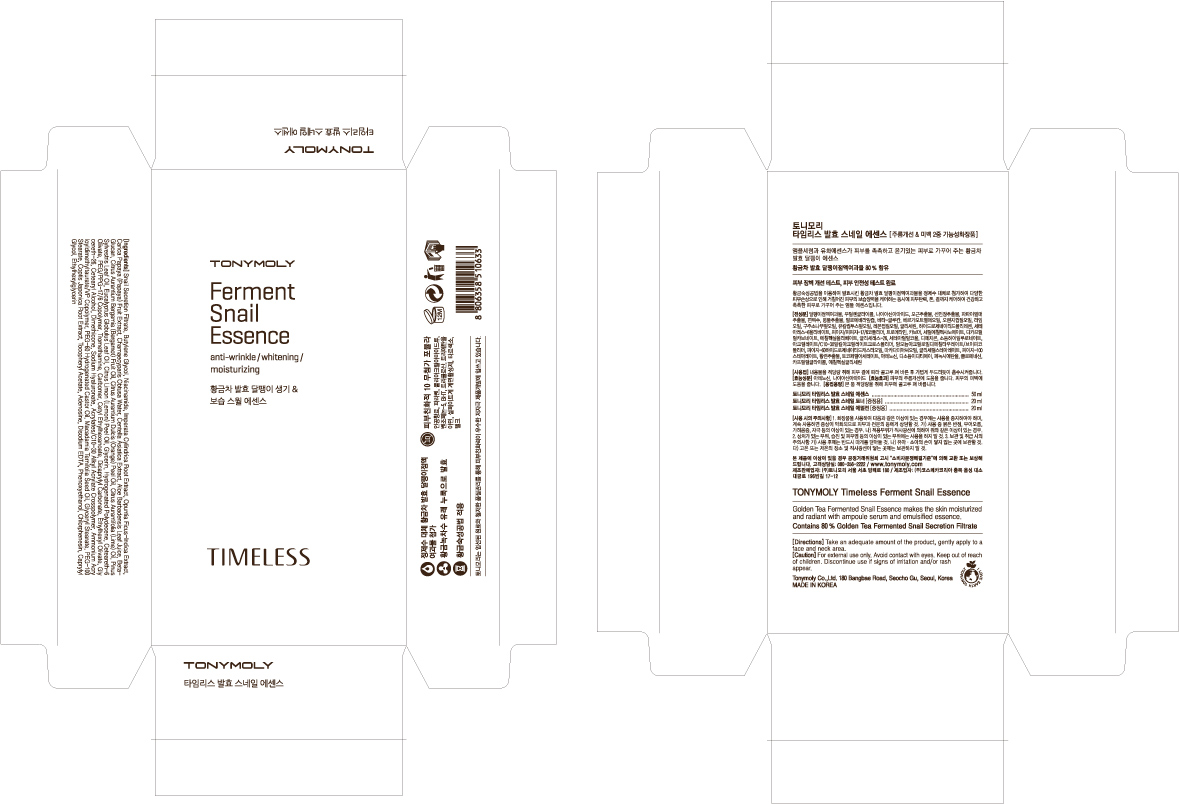 DRUG LABEL: TONYMOLY Timeless Ferment Snail Essence
NDC: 59078-102 | Form: LOTION
Manufacturer: Tonymoly Co., Ltd.
Category: otc | Type: HUMAN OTC DRUG LABEL
Date: 20160202

ACTIVE INGREDIENTS: GLYCERIN 503 mg/50 mL
INACTIVE INGREDIENTS: ORANGE PEEL; LEMON PEEL; COPTIS JAPONICA ROOT; PEG-60 HYDROGENATED CASTOR OIL; DICAPRYLYL CARBONATE; TROMETHAMINE; SODIUM BENZOATE; WATER; BUTYLENE GLYCOL; NIACINAMIDE; CETEARETH-6 OLIVATE; PEG/PPG-17/6 COPOLYMER; CETYL ETHYLHEXANOATE; PHENOXYETHANOL; GLYCERETH-26; DIMETHICONE; CHLORPHENESIN; ETHYLHEXYLGLYCERIN; CAPRYLYL GLYCOL; AMMONIUM ACRYLOYLDIMETHYLTAURATE/VP COPOLYMER; PEG-100 STEARATE; ADENOSINE; PROPANEDIOL; EDETATE DISODIUM; ALCOHOL; LIME OIL; PINE NEEDLE OIL (PINUS SYLVESTRIS); HYALURONATE SODIUM; EUCALYPTUS GLOBULUS LEAF; CHAMAECYPARIS OBTUSA WHOLE; IMPERATA CYLINDRICA ROOT; OPUNTIA FICUS-INDICA; POLYETHYLENE GLYCOL 400; CENTELLA ASIATICA; PAPAYA; ALOE VERA LEAF; BERGAMOT OIL

Active Ingredients

Glycerin 0.80%

Purpose

Skin Protectant

Dosage

Apply a small amount of this product.

Caution

For external use only. Avoid contact with eyes. Keep out of reach of children. Discontinue use if signs of irritation and/or rash appear.

Keep out of reach of children. Discontinue use if signs of irritation and/or rash appear.

Direction

Take an adequate amount of the product, gently apply to a face and neck area.

After emulsion, apply evenly across the face.

Inactive Ingredients

Water, Butylene Glycol, Niacinamide, Ceteareth-6 Olivate, PEG/PPG-17/6 Copolymer, Hydrogenated Polydecene, Ethylhexyl Olivate, Cetyl Ethylhexanoate, Dicaprylyl Carbonate, Phenoxyethanol, Carbomer, Tromethamine, PEG-60 Hydrogenated Castor Oil, Glycereth-26, Cetearyl Alcohol, Dimethicone, Acrylates/C10-30 Alkyl Acrylate Crosspolymer, Chlorphenesin, Snail Secretion Filtrate, Macadamia Ternifolia Seed Oil, Ethylhexylglycerin, Caprylyl Glycol, Ammonium Acryloyldimethyltaurate/VP Copolymer, Glyceryl Stearate, PEG-100 Stearate, Tocopheryl Acetate, Adenosine, Disodium EDTA, Citrus Limon (Lemon) Peel Oil, Coptis Japonica Root Extract, Citrus Aurantium Bergamia (Bergamot) Fruit Oil, Alcohol, Citrus aurantium dulcis (orange) peel oil, Citrus Aurantifolia (Lime) Oil, Pinus Sylvestris Leaf Oil, Sodium Hyaluronate, Eucalyptus Globulus Leaf Oil, Chamaecyparis Obtusa Water, Imperata Cylindrica Root Extract, Opuntia Ficus-Indica Extract, Propanediol, PEG-8, Centella Asiatica Extract, Carica papaya (papaya) fruit Extract, Aloe Barbadensis Leaf Juice, Beta-Glucan, Potassium sorbate, Sodium Benzoate